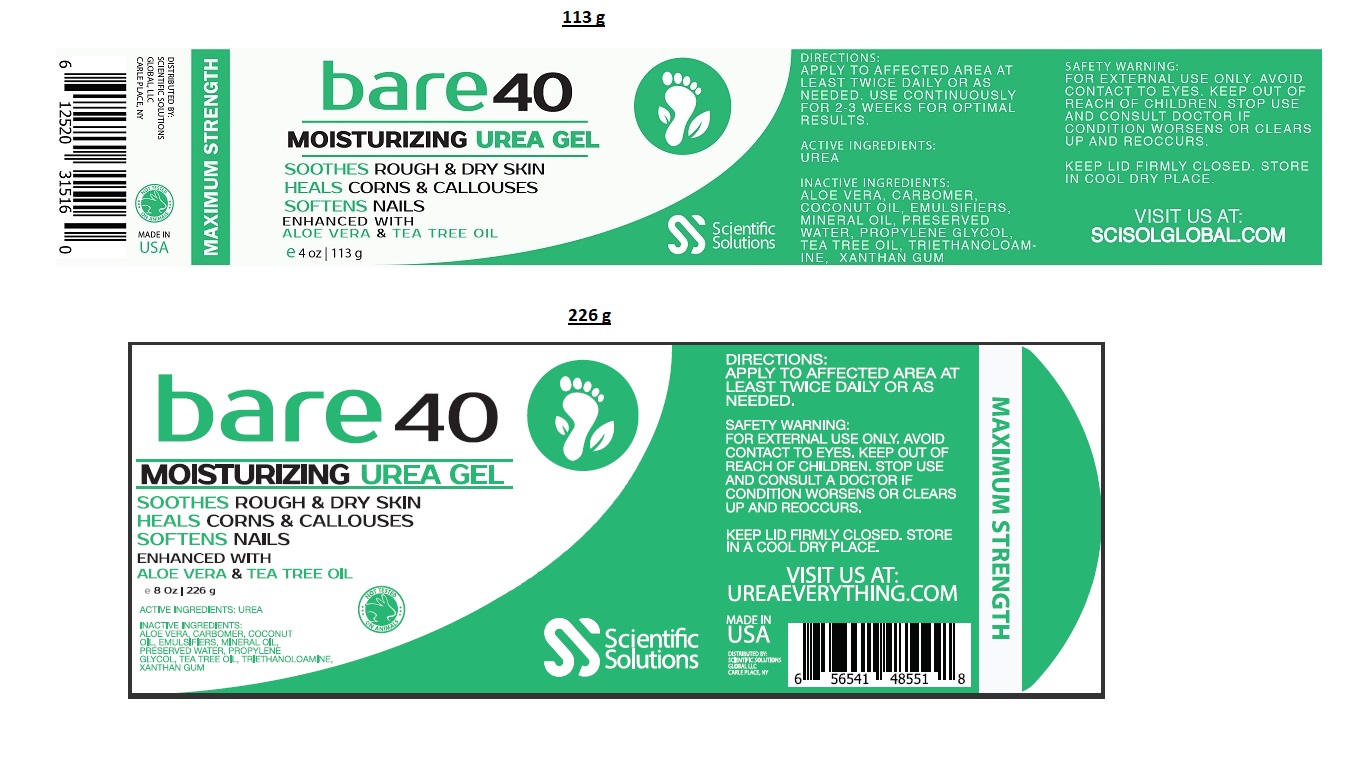 DRUG LABEL: Bare 40
NDC: 71718-002 | Form: GEL
Manufacturer: Scientific Solutions Global, LLC
Category: otc | Type: HUMAN OTC DRUG LABEL
Date: 20180322

ACTIVE INGREDIENTS: UREA 40 g/100 g
INACTIVE INGREDIENTS: TEA TREE OIL; ALOE VERA LEAF; CARBOXYPOLYMETHYLENE; XANTHAN GUM; MINERAL OIL; PROPYLENE GLYCOL; TROLAMINE; COCONUT OIL; WATER; TRIDECETH-10

BARE 40 urea gel

ACTIVE INGREDIENTS:

UREA

PURPOSE

HEALS CORNS & CALLUSES

INDICATIONS AND USAGE

SOOTHES ROUGH & DRY SKIN

SOFTEN NAILS

MOISTURIZING GEL

SAFETY WARNING :

FOR EXTERNAL USE ONLY. AVOID CONTACT TO EYES.

STOP USE AND CONSULT DOCTOR IF CONDITION WORSENS OR CLEARS UP AND REOCCURS.

KEEP OUT OF REACH OF CHILDREN.

DIRECTIONS:

APPLY TO AFFECTED AREA AT LEAST TWICE DAILY OR AS NEEDED.

USE CONTINUOUSLY FOR 2-3 WEEKS FOR OPTIMAL RESULTS.

INACTIVE INGREDIENTS :

TEA TREE OIL, ALOE VERA, CARBOMER, XANTHAN GUM, MINERAL OIL, PROPYLENE GLYCOL,TRIETHANOLAMINE, EMULSIFIERS, COCONUT OIL, PRESERVED WATER

STORAGE AND HANDLING

KEEP LID FIRMLY CLOSED. STORE IN COOL DRY PLACE.

ENHANCED WITH ALOE VERA & TEA TREE OIL

MAXIMUM STRENGTH

VISIT US AT : UREAEVERYTHING.COM